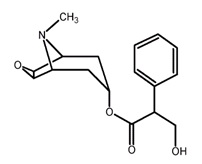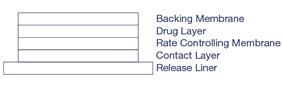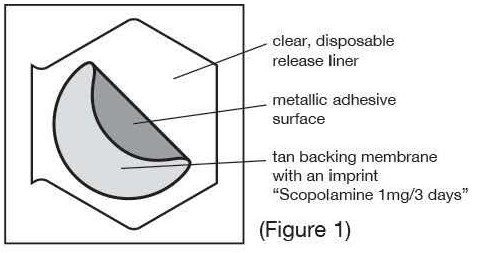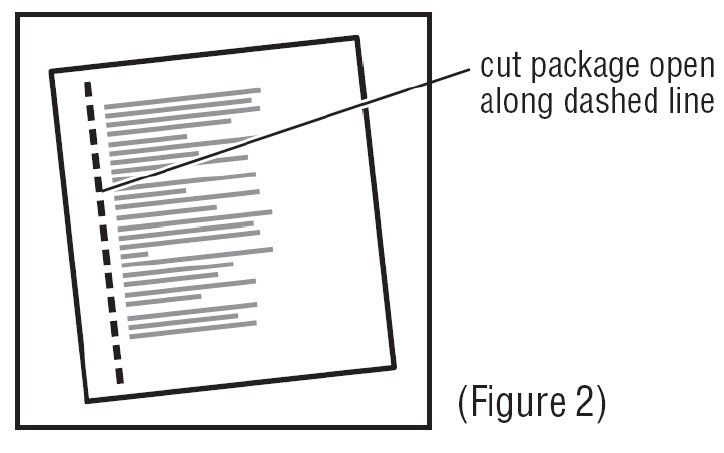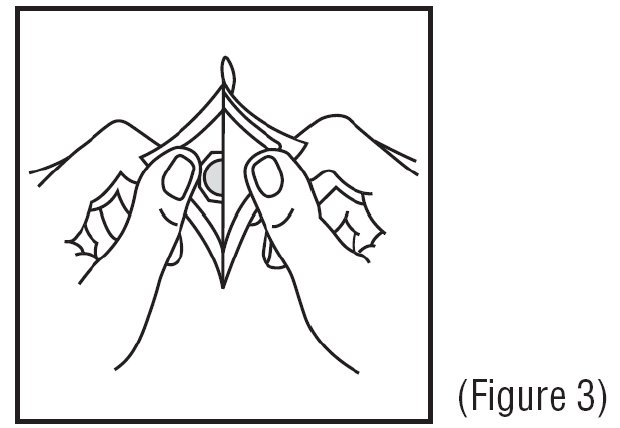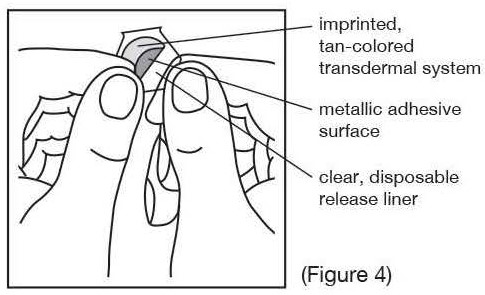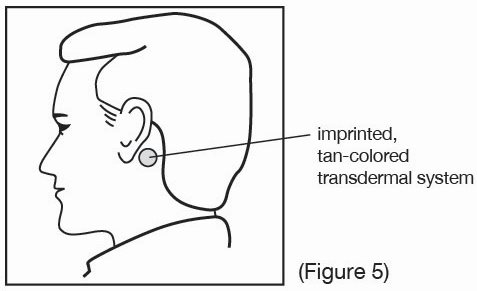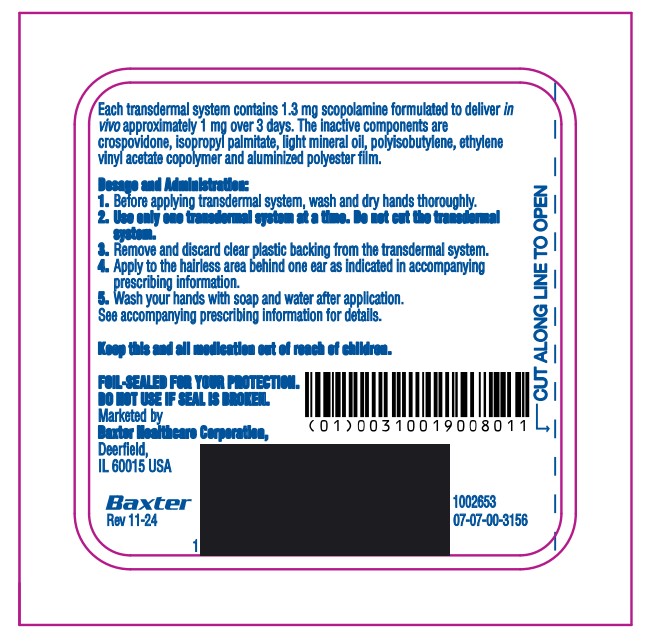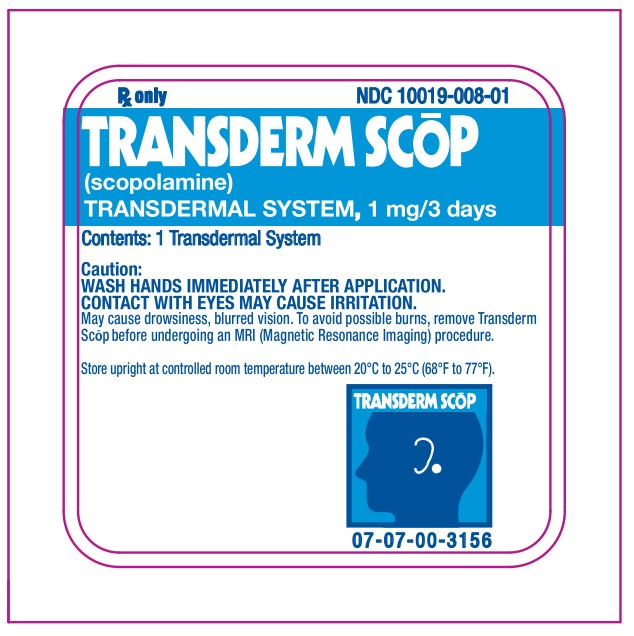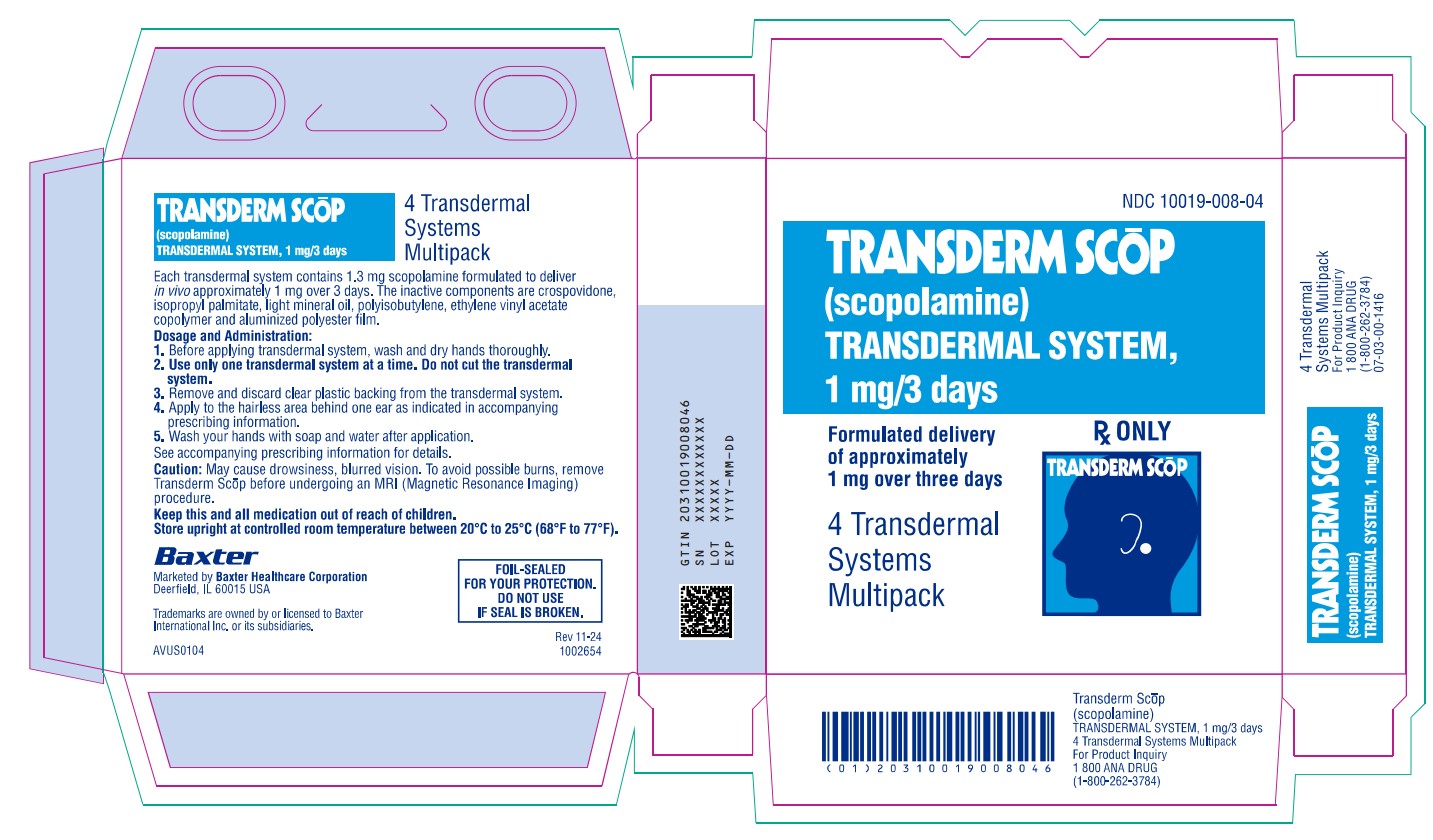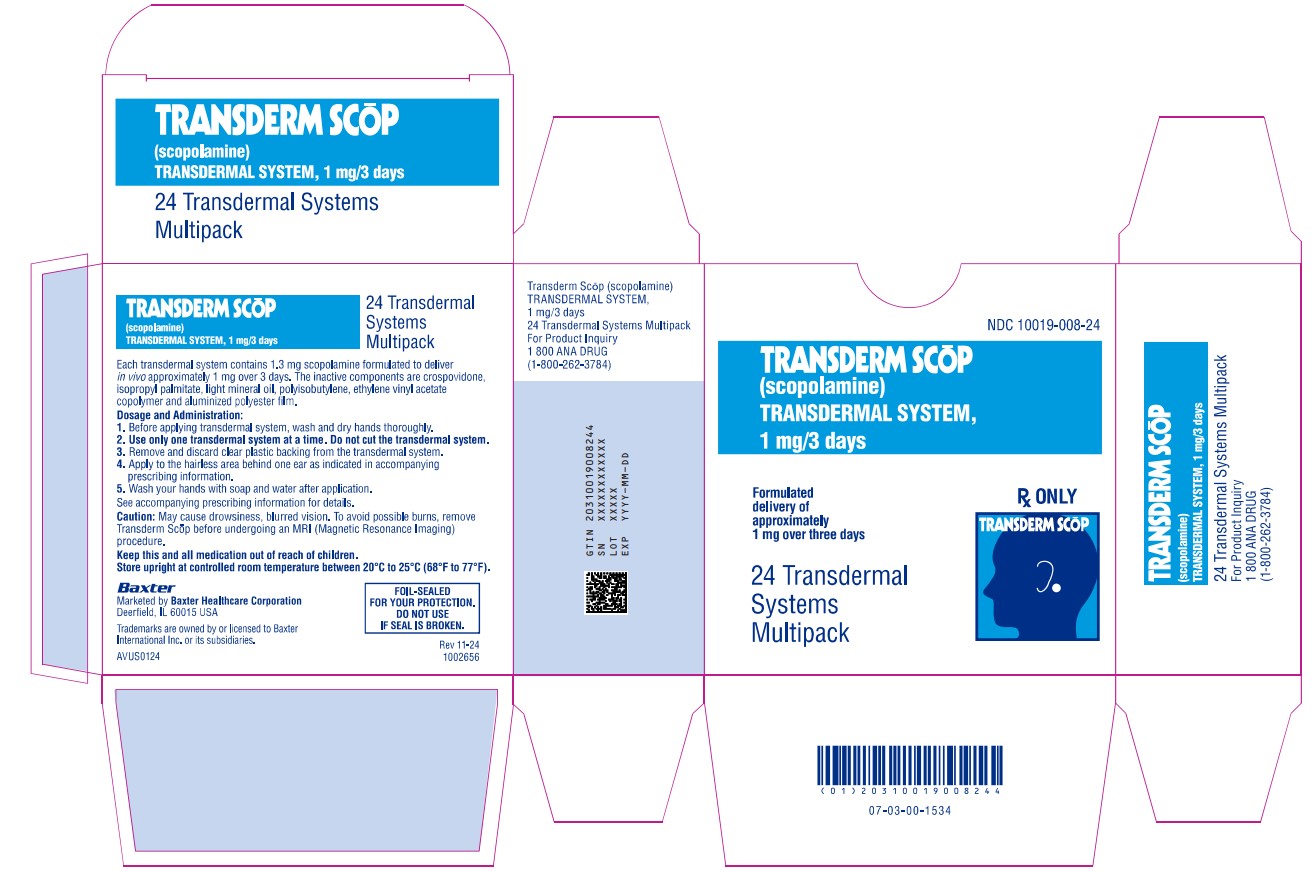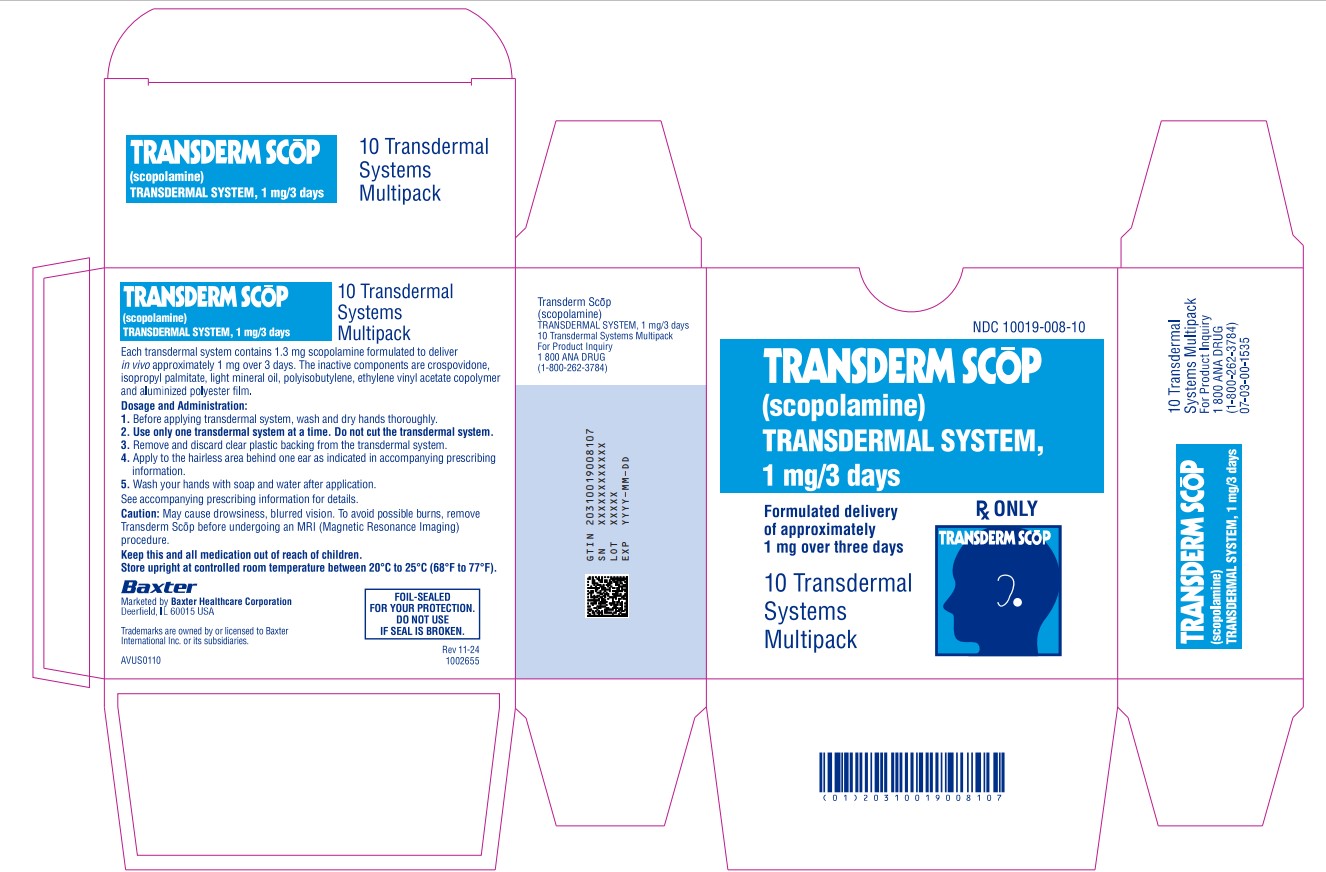 DRUG LABEL: Transderm Scop
NDC: 10019-553 | Form: PATCH, EXTENDED RELEASE
Manufacturer: Baxter Healthcare Corporation
Category: prescription | Type: HUMAN PRESCRIPTION DRUG LABEL
Date: 20250610

ACTIVE INGREDIENTS: SCOPOLAMINE 1 mg/3 d
INACTIVE INGREDIENTS: POLYISOBUTYLENE (1100000 MW); POLYISOBUTYLENE (35000 MW); LIGHT MINERAL OIL

HIGHLIGHTS OF PRESCRIBING INFORMATION

These highlights do not include all the information needed to use TRANSDERM SCŌP safely and effectively. See full prescribing information for TRANSDERM SCŌP.
TRANSDERM SCŌP (scopolamine transdermal system)
Initial U.S. Approval: 1979

RECENT MAJOR CHANGES

Warnings and Precautions, Hyperthermia (5.5) 4/2025

1 INDICATIONS AND USAGE

TRANSDERM SCŌP is an anticholinergic indicated in adults for the prevention of:

- nausea and vomiting associated with motion sickness. (1)
- post-operative nausea and vomiting (PONV) associated with recovery from anesthesia and/or opiate analgesia and surgery. (1)

2 DOSAGE AND ADMINISTRATION

Application and Removal (2.1):

- Each TRANSDERM SCŌP transdermal system delivers 1 mg of scopolamine over 3 days.
- Only wear one transdermal system at a time.
- Do not cut the transdermal system.
- Wash hands thoroughly with soap and water after application.
- Avoid touching or applying pressure to the transdermal system once applied.
- Upon removal, fold used transdermal system in half with sticky side together, discard to prevent accidental contact or ingestion, and wash the hands and application site with soap and water.

Recommended Dosage:

- Motion Sickness: Apply one transdermal system to the hairless area behind one ear at least 4 hours before antiemetic effect is required for use up to 3 days. If therapy for more than 3 days is required, remove the first transdermal system and apply a new transdermal system behind the other ear. (2.2)
- PONV: For surgeries other than cesarean section, apply one transdermal system behind the ear the evening before surgery and remove 24 hours following surgery. (2.2)

3 DOSAGE FORMS AND STRENGTHS

Transdermal system: 1 mg/3 days (3)

4 CONTRAINDICATIONS

- Angle closure glaucoma. (4, 6.2)
- Hypersensitivity to scopolamine or other belladonna alkaloids or to any ingredient or component of the formulation or delivery system. (4, 7)

5 WARNINGS AND PRECAUTIONS

- Acute Angle Closure Glaucoma: Monitor for increased intraocular pressure in patients with open-angle glaucoma and adjust glaucoma therapy as needed. Discontinue if signs or symptoms of acute angle closure glaucoma develop. (5.1)
- Neuropsychiatric Adverse Reactions: May cause psychiatric and cognitive effects, seizures and impair mental and/or physical abilities. Monitor patients for new or worsening psychiatric symptoms during treatment and during concomitant treatment with other drugs that are associated with similar psychiatric effects. (5.2, 7.1)
- Eclamptic Seizures in Pregnant Women: Avoid use in patients with severe preeclampsia. (5.3)
- Gastrointestinal and Urinary Disorders: Consider more frequent monitoring during treatment in patients suspected of having intestinal obstruction; patients with pyloric obstruction, patients with impeded urine flow or receiving other anticholinergic drugs. Discontinue if patient develops difficulty in urination. (5.4, 7.2)
- Hyperthermia: Serious adverse reactions have been reported postmarketing in adult and pediatric patients, including fatal cases. If symptoms occur, remove the transdermal system, and contact a healthcare provider. (5.5)
- Drug Withdrawal/Post-Removal Symptoms: Anticholinergic symptoms may occur 24 hours or more after removal of the transdermal system. (5.6)
- Blurred Vision: Avoid contact with the eyes. (2.1, 5.7)
- Magnetic Resonance Imaging (MRI) Skin Burns: Remove TRANSDERM SCŌP prior to MRI scan. (5.8)

6 ADVERSE REACTIONS

Most common adverse reactions are:

- Motion Sickness (>15%): dry mouth, drowsiness, blurred vision and dilation of the pupils. (6.1)
- PONV (≥ 3%): dry mouth, dizziness, somnolence, agitation, visual impairment, confusion, mydriasis and pharyngitis. (6.1)

To report SUSPECTED ADVERSE REACTIONS, contact Baxter Healthcare Corporation at 1-866-888-2472 or FDA at 1-800-FDA-1088 or www.fda.gov/medwatch.

7 DRUG INTERACTIONS

- Drugs Causing Central Nervous System (CNS) Adverse Reactions: Monitor patients for CNS adverse reactions (drowsiness, dizziness or disorientations). (7.1)
- Anticholinergic Drugs: Consider more frequent monitoring during treatment in patients receiving other anticholinergic drugs. (7.2)
- Oral Drugs Absorbed in the Stomach: Monitor for increased or decreased therapeutic effect of the oral drug. (7.3)
- Interaction with Gastric Secretion Test: Discontinue use of TRANSDERM SCŌP 10 days prior to testing. (7.4)

8 USE IN SPECIFIC POPULATIONS

- Geriatric Patients: Consider more frequent monitoring during treatment due to increased risk of CNS adverse reactions. (5.2, 8.5)
- Renal or Hepatic Impairment: Consider more frequent monitoring during treatment due to increased risk of CNS adverse reactions. (5.2, 8.6)

FULL PRESCRIBING INFORMATION

1 INDICATIONS AND USAGE

TRANSDERM SCŌP is indicated in adults for the prevention of:

- nausea and vomiting associated with motion sickness.
- post-operative nausea and vomiting (PONV) associated with recovery from anesthesia and/or opiate analgesia and surgery.

2 DOSAGE AND ADMINISTRATION

2.1 Important Application and Removal Instructions

- Each TRANSDERM SCŌP transdermal system is formulated to deliver in vivo approximately 1 mg of scopolamine over 3 days.
- Only wear one transdermal system at any time.
- Do not cut the transdermal system.
- Apply the transdermal system to the skin in the postauricular area (hairless area behind one ear).
- After the transdermal system is applied on the dry skin behind the ear, wash hands thoroughly with soap and water and dry hands [see Warnings and Precautions (5.7)].
- If the transdermal system becomes displaced, discard the transdermal system, and apply a new transdermal system on the hairless area behind the other ear.
- Once the transdermal system has been affixed, avoid touching or applying pressure to the transdermal system while it is being worn, since pressure exerted on it may cause scopolamine to ooze out at the edge.
- Upon removal, fold the used transdermal system in half with the sticky side together, and discard in household trash in a manner that prevents accidental contact or ingestion by children, pets or others.
- Wash the hands and application site with soap and water after transdermal system removal [see Warnings and Precautions (5.7)].

2.2 Recommended Adult Dosage

Motion Sickness

Apply one TRANSDERM SCŌP transdermal system to the hairless area behind one ear at least 4 hours before the antiemetic effect is required – for use up to 3 days. If therapy is required for longer than 3 days, remove the first transdermal system and apply a new TRANSDERM SCŌP transdermal system behind the other ear.

PONV

For surgeries other than cesarean section: Apply one TRANSDERM SCŌP transdermal system the evening before scheduled surgery. Remove the transdermal system 24 hours following surgery.

3 DOSAGE FORMS AND STRENGTHS

Transdermal system: a circular, flat, tan-colored transdermal system imprinted with “SCOP 1 mg/3 days”

4 CONTRAINDICATIONS

TRANSDERM SCŌP is contraindicated in patients with:

- angle closure glaucoma [see Warnings and Precautions (5.1)].
- hypersensitivity to scopolamine or other belladonna alkaloids or to any ingredient or component in the formulation or delivery system. Reactions have included rash generalized and erythema [see Adverse Reactions (6.2), Description (11)].

5 WARNINGS AND PRECAUTIONS

5.1 Acute Angle Closure Glaucoma

The mydriatic effect of scopolamine may cause an increase in intraocular pressure resulting in acute angle closure glaucoma. Monitor intraocular pressure in patients with open angle glaucoma and adjust glaucoma therapy during TRANSDERM SCŌP use, as needed. Advise patients to immediately remove the transdermal system and contact their healthcare provider if they experience symptoms of acute angle closure glaucoma (e.g., eye pain or discomfort, blurred vision, visual halos or colored images in association with red eyes from conjunctival congestion and corneal edema).

5.2 Neuropsychiatric Adverse Reactions

Psychiatric Adverse Reactions

Scopolamine has been reported to exacerbate psychosis. Other psychiatric reactions have also been reported, including acute toxic psychosis, agitation, speech disorder, hallucinations, paranoia, and delusions [see Adverse Reactions (6.2)]. Monitor patients for new or worsening psychiatric symptoms during treatment with TRANSDERM SCŌP. Also, monitor patients for new or worsening psychiatric symptoms during concomitant treatment with other drugs that are associated with similar psychiatric effects [see Drug Interactions (7.1)]. In cases of psychiatric reactions occurring TRANSDERM SCŌP should be removed at once. If, despite this, the symptoms persist in a severe form, instruct patients to seek medical attention.

Seizures

Seizures and seizure-like activity have been reported in patients receiving scopolamine. Weigh this potential risk against the benefits before prescribing TRANSDERM SCŌP to patients with a history of seizures, including those receiving anti-epileptic medication or who have risk factors that can lower the seizure threshold.

Cognitive Adverse Reactions

Scopolamine can cause drowsiness, disorientation, and confusion. Discontinue TRANSDERM SCŌP if signs or symptoms of cognitive impairment develop. If, despite this, the symptoms persist in a severe form, instruct patients to seek medical attention. Elderly and pediatric patients may be more sensitive to the neurological and psychiatric effects of TRANSDERM SCŌP. Consider more frequent monitoring during treatment with TRANSDERM SCŌP in elderly patients [see Use in Specific Populations (8.5)]. TRANSDERM SCŌP is not approved for use in pediatric patients [see Use in Specific Populations (8.4)].

Hazardous Activities

TRANSDERM SCŌP may impair the mental and/or physical abilities required for the performance of hazardous tasks such as driving a motor vehicle, operating machinery or participating in underwater sports. Concomitant use of other drugs that cause central nervous system (CNS) adverse reactions (e.g., alcohol, sedatives, hypnotics, opiates, and anxiolytics) or have anticholinergic properties (e.g., other belladonna alkaloids, sedating antihistamines, meclizine, tricyclic antidepressants, and muscle relaxants) may increase this effect [see Drug Interactions (7.1)]. Inform patients not to operate motor vehicles or other dangerous machinery or participate in underwater sports until they are reasonably certain that TRANSDERM SCŌP does not affect them adversely.

5.3 Eclamptic Seizures in Pregnant Women

Eclamptic seizures have been reported in pregnant women with severe preeclampsia soon after injection of intravenous and intramuscular scopolamine [see Use in Specific Populations (8.1)]. Avoid use of TRANSDERM SCŌP in patients with severe preeclampsia.

5.4 Gastrointestinal and Urinary Disorders

Scopolamine, due to its anticholinergic properties, can decrease gastrointestinal motility and cause urinary retention. Consider more frequent monitoring during treatment with TRANSDERM SCŌP in patients suspected of having intestinal obstruction, patients with pyloric obstruction or patients with impeded flow of urine (e.g., in diseases of the prostate or urinary bladder neck obstruction) and patients receiving other anticholinergic drugs [see Drug Interactions (7.2)]. Discontinue TRANSDERM SCŌP in patients who develop difficulty in urination.

5.5 Hyperthermia

Serious adverse reactions of hyperthermia have been reported postmarketing in adult and pediatric patients receiving transdermal scopolamine, including fatal cases. Anticholinergic agents, including scopolamine, can increase core body temperature and reduce sweating, which may cause further increases in body temperature. Hyperthermia may be exacerbated by exposure to external heat sources or high environmental temperature. Pediatric and geriatric patients may be more susceptible to these anticholinergic effects on thermoregulation. Advise patients if body temperature increases, or they are not sweating in warm environmental conditions, to remove the transdermal system and contact their healthcare provider. Symptoms may persist following removal of the used transdermal system as there may be continued systemic absorption of scopolamine through the skin. TRANSDERM SCŌP is not approved for use in pediatric patients [see Use in Specific Populations (8.4, 8.5)].

5.6 Drug Withdrawal/Post-Removal Symptoms

Discontinuation of TRANSDERM SCŌP, usually after several days of use, may result in withdrawal symptoms, such as disturbances of equilibrium, dizziness, nausea, vomiting, abdominal cramps, sweating, headache, mental confusion, muscle weakness, bradycardia and hypotension. The onset of these symptoms is generally 24 hours or more after the transdermal system has been removed. Instruct patients to seek medical attention if they experience severe symptoms.

5.7 Blurred Vision

Scopolamine can cause temporary dilation of the pupils resulting in blurred vision if it comes in contact with the eyes.

Advise patients to wash their hands thoroughly with soap and water and dry their hands immediately after handling the transdermal system, do not touch the system while wearing it, and wash hands and the application site with soap and water after transdermal system removal [see Dosage and Administration (2.1)].

5.8 Magnetic Resonance Imaging (MRI) Skin Burns

TRANSDERM SCŌP contains an aluminized membrane. Skin burns have been reported at the application site in patients wearing an aluminized transdermal system during an MRI scan. Remove TRANSDERM SCŌP before undergoing an MRI.

6 ADVERSE REACTIONS

The following serious adverse reactions are described elsewhere in labeling:

- Acute Angle Closure Glaucoma [see Warnings and Precautions (5.1)]
- Neuropsychiatric Adverse Reactions [see Warnings and Precautions (5.2)]
- Eclamptic Seizures in Pregnant Women [see Warnings and Precautions (5.3)]
- Gastrointestinal and Urinary Disorders [see Warnings and Precautions (5.4)]
- Hyperthermia [see Warnings and Precautions (5.5)]
- Drug Withdrawal/Post-Removal Symptoms [see Warnings and Precautions (5.6)]
- Blurred Vision [see Warnings and Precautions (5.7)]
- MRI Skin Burns [see Warnings and Precautions (5.8)]

6.1 Clinical Trials Experience

Because clinical trials are conducted under widely varying conditions, adverse reaction rates observed in the clinical trials of a drug cannot be directly compared to rates in the clinical trials of another drug and may not reflect the rates observed in practice.

Motion Sickness

The most common adverse reaction (approximately two thirds) was dry mouth. Less common adverse reactions, included drowsiness (less than one sixth), blurred vision and dilation of the pupils.

PONV

Common adverse reactions, occurring in at least 3% of patients in PONV clinical trials are shown in Table 1.

Table 1 Common Adverse Reactions* in Surgical Patients for the Prevention of PONV
 | TRANSDERM SCŌP % (N = 461) | Placebo % (N = 457)
Dry mouth | 29 | 16
Dizziness | 12 | 7
Somnolence | 8 | 4
Agitation | 6 | 4
Visual Impairment | 5 | 3
Confusion | 4 | 3
Mydriasis | 4 | 0
Pharyngitis | 3 | 2
*occurring in at least 3% of patients and at a rate higher than placebo

6.2 Postmarketing Experience

The following adverse reactions have been identified during post-approval use of scopolamine transdermal system. Because these reactions are reported voluntarily from a population of uncertain size, it is not always possible to reliably estimate their frequency or establish a causal relationship to drug exposure.

Psychiatric disorders: acute psychosis including: disorientation, hallucinations, and paranoia

Nervous system disorders: amnesia, coordination abnormalities, disturbance in attention, headache, restlessness, speech disorder

General disorders and administration site conditions: application site reactions (including blistering, burning, pruritus, and rash) and hyperthermia

Eye disorders: amblyopia, angle closure glaucoma, dry eyes, eyelid irritation, eye pruritus

Skin and subcutaneous tissue disorders: erythema, rash generalized, skin irritation

Renal and urinary disorders: dysuria

Ear and labyrinth disorders: vertigo

7 DRUG INTERACTIONS

7.1 Drugs Causing Central Nervous System (CNS) Adverse Reactions

The concurrent use of TRANSDERM SCŌP with other drugs that cause CNS adverse reactions of drowsiness, dizziness or disorientation (e.g., sedatives, hypnotics, opiates, anxiolytics and alcohol) or have anticholinergic properties (e.g., other belladonna alkaloids, sedating antihistamines, meclizine, tricyclic antidepressants, and muscle relaxants) may potentiate the effects of TRANSDERM SCŌP [see Warnings and Precautions (5.2)]. Either TRANSDERM SCŌP or the interacting drug should be chosen, depending on the importance of the drug to the patient. If the interacting drug cannot be avoided, monitor patients for CNS adverse reactions.

7.2 Anticholinergic Drugs

Concomitant use of scopolamine with other drugs having anticholinergic properties may increase the risk of CNS adverse reactions [see Drug Interactions (7.1)], intestinal obstruction and/or urinary retention. Consider more frequent monitoring during treatment with TRANSDERM SCŌP in patients receiving anticholinergic drugs [see Warnings and Precautions (5.2, 5.4)].

7.3 Oral Drugs Absorbed in the Stomach

TRANSDERM SCŌP, as an anticholinergic, may delay gastric and upper gastrointestinal motility and, therefore, the rate of absorption of other orally administered drugs. Monitor patients for modified therapeutic effect of concomitant orally administered drugs with a narrow therapeutic index.

7.4 Interaction with Gastric Secretion Test

Scopolamine will interfere with the gastric secretion test. Discontinue TRANSDERM SCŌP 10 days prior to testing.

8 USE IN SPECIFIC POPULATIONS

8.1 Pregnancy

Risk Summary

Eclamptic seizures have been reported in pregnant women with severe preeclampsia soon after injection of intravenous or intramuscular scopolamine. Avoid use of TRANSDERM SCOP in patients with severe preeclampsia [see Warnings and Precautions (5.3) and Data]. Available data from observational studies and postmarketing reports with scopolamine use in pregnant women have not identified a drug associated risk of major birth defects, miscarriage, or adverse fetal outcomes.

In animal studies, there was no evidence of adverse developmental effects with intravenous administration of scopolamine hydrobromide revealed in rats. Embryotoxicity was observed in rabbits at intravenous doses producing plasma levels approximately 100 times the levels achieved in humans using a transdermal system.

The background risk of major birth defects and miscarriage for the indicated population is unknown. All pregnancies have a background risk of birth defect, loss, or other adverse outcomes. In the U.S. general population, the background risk of major birth defects and miscarriage in clinically recognized pregnancies is 2% to 4% and 15% to 20%, respectively.

Data

Human Data

In published case reports, two pregnant patients with severe preeclampsia were administered intravenous and intramuscular scopolamine, respectively, and developed eclamptic seizures soon after scopolamine administration [see Warnings and Precautions (5.3)].

Animal Data

In animal reproduction studies, when pregnant rats and rabbits received scopolamine hydrobromide by daily intravenous injection, no adverse effects were observed in rats. An embryotoxic effect was observed in rabbits at doses producing plasma levels approximately 100 times the levels achieved in humans using a transdermal system. Scopolamine administered parenterally to rats and rabbits at doses higher than the dose delivered by TRANSDERM SCŌP did not affect uterine contractions or increase the duration of labor.

8.2 Lactation

Risk Summary

Scopolamine is present in human milk. There are no available data on the effects of scopolamine on the breastfed infant or the effects on milk production. The developmental and health benefits of breastfeeding should be considered along with the mother’s clinical need for TRANSDERM SCŌP and any potential adverse effects on the breastfed child from TRANSDERM SCŌP or from the underlying maternal condition.

8.4 Pediatric Use

The safety and effectiveness of TRANSDERM SCŌP have not been established in pediatric patients. Pediatric patients are particularly susceptible to the anticholinergic adverse reactions of scopolamine, including neurologic and psychiatric adverse reactions and drug withdrawal syndrome. Serious adverse reactions of acute psychosis (e.g., disorientation, hallucinations), amblyopia, hyperthermia (including a fatal case), and mydriasis have also been reported in pediatric patients [see Warnings and Precautions (5.2, 5.5)].

8.5 Geriatric Use

Clinical trials of TRANSDERM SCŌP did not include sufficient number of subjects aged 65 years and older to determine if they respond differently from younger subjects. In other clinical experience, elderly patients had an increased risk of neurologic and psychiatric adverse reactions, such as hallucinations, confusion, dizziness and drug withdrawal syndrome [see Warnings and Precautions (5.2, 5.6)]. Consider more frequent monitoring for CNS adverse reactions during treatment with TRANSDERM SCŌP in geriatric patients [see Warnings and Precautions (5.2)].

Serious adverse reactions of hyperthermia have been reported postmarketing in geriatric patients receiving transdermal scopolamine, including a fatal case. Geriatric patients may be more susceptible to the anticholinergic effects of disruption in thermoregulation. Advise patients if body temperature increases, or they are not sweating in warm environmental conditions, to remove the transdermal system and contact their healthcare provider [see Warnings and Precautions (5.5)].

8.6 Renal or Hepatic Impairment

TRANSDERM SCŌP has not been studied in patients with renal or hepatic impairment. Consider more frequent monitoring during treatment with TRANSDERM SCŌP in patients with renal or hepatic impairment because of the increased risk of CNS adverse reactions [see Warnings and Precautions (5.2)].

9 DRUG ABUSE AND DEPENDENCE

9.1 Controlled Substance

TRANSDERM SCŌP contains scopolamine, which is not a controlled substance.

9.3 Dependence

Termination of TRANSDERM SCŌP, usually after several days of use, may result in withdrawal symptoms such as disturbances of equilibrium, dizziness, nausea, vomiting, abdominal cramps, sweating, headache, mental confusion, muscle weakness, bradycardia and hypotension. These withdrawal symptoms indicate that scopolamine, like other anticholinergic drugs, may produce physical dependence. The onset of these symptoms, generally 24 hours or more after the transdermal system has been removed, can be severe and may require medical intervention [see Warnings and Precautions (5.6)].

10 OVERDOSAGE

Anticholinergic toxicity includes both central and peripheral signs and symptoms: agitation, central nervous system effects (e.g., coma, confusion, hallucinations, lethargy, seizures, somnolence), decreased bowel sounds, dry flushed skin, dry mouth, hyperthermia, hypertension, supraventricular arrhythmias, tachycardia, urinary retention, visual disturbances (e.g., amblyopia, mydriasis). These symptoms can be severe and may require medical intervention.

In cases of toxicity remove the TRANSDERM SCŌP transdermal system. Serious symptomatic cases of overdosage involving multiple transdermal system applications and/or ingestion may be managed by initially ensuring the patient has an adequate airway and supporting respiration and circulation. This should be rapidly followed by removal of all transdermal systems from the skin and the mouth. If there is evidence of transdermal system ingestion, endoscopic removal of swallowed transdermal systems, or administration of activated charcoal should be considered, as indicated by the clinical situation. In any case where there is serious overdosage or signs of evolving acute toxicity, continuous monitoring of vital signs and ECG, establishment of intravenous access, and administration of oxygen are all recommended.

The signs and symptoms of overdose/toxicity due to scopolamine should be carefully distinguished from the occasionally observed syndrome of withdrawal [see Warnings and Precautions (5.6)]. Although mental confusion and dizziness may be observed with both acute toxicity and withdrawal, other characteristic findings differ: tachyarrhythmias, dry skin, and decreased bowel sounds suggest anticholinergic toxicity, while bradycardia, headache, nausea and abdominal cramps, and sweating suggest post-removal withdrawal.

If over-exposure occurs, call the Poison Help line at 1-800-222-1222 for current information on the management of poisoning or overdosage.

11 DESCRIPTION

TRANSDERM SCŌP (scopolamine transdermal system) is designed for continuous release of scopolamine following application to an area of intact skin on the head, behind the ear. Each system contains 1.3 mg of scopolamine base. Scopolamine is (9-methyl-3-oxa-9-azatricyclo[3.3.1.0^2,4]nonan-7-yl) 3-hydroxy-2-phenylpropanoate. The empirical formula is C17H21NO4 and its structural formula is:

Scopolamine has a molecular weight of 303.35 and a pKa of 7.55-7.81. The TRANSDERM SCŌPtransdermal system is a circular, 0.2 mm thick, 2.5 cm^2 film with four layers. Proceeding from the visible surface towards the surface attached to the skin, these layers are: (1) a backing membrane of tan-colored, aluminized, polyester film; (2) a drug layer of scopolamine, crospovidone, isopropyl palmitate, light mineral oil, and polyisobutylene; (3) an ethylene vinyl acetate copolymer membrane that controls the rate of delivery of scopolamine from the system to the skin surface; and (4) a contact layer formulation of crospovidone, isopropyl palmitate, light mineral oil, polyisobutylene, and scopolamine. A release liner of siliconized polyester, which covers the adhesive layer, is removed before the system is used.

Cross section of the system:

12 CLINICAL PHARMACOLOGY

12.1 Mechanism of Action

Scopolamine, a belladonna alkaloid, is an anticholinergic. Scopolamine acts: i) as a competitive inhibitor at postganglionic muscarinic receptor sites of the parasympathetic nervous system, and ii) on smooth muscles that respond to acetylcholine but lack cholinergic innervation. It has been suggested that scopolamine acts in the central nervous system (CNS) by blocking cholinergic transmission from the vestibular nuclei to higher centers in the CNS and from the reticular formation to the vomiting center. Scopolamine can inhibit the secretion of saliva and sweat, decrease gastrointestinal secretions and motility, cause drowsiness, dilate the pupils, increase heart rate, and depress motor function.

12.3 Pharmacokinetics

The system is formulated to deliver approximately 1 mg of scopolamine to the systemic circulation over 3 days.

Absorption
Following application to the skin behind the ear, circulating plasma concentrations are detected within 4 hours with peak concentrations being obtained, on average, within 24 hours. The average plasma concentration produced is 87 pg/mL (0.28 nM) for free scopolamine and 354 pg/mL for total scopolamine (free + conjugates). Following removal of the used transdermal system, there is some degree of continued systemic absorption of scopolamine bound in the skin layers.

Distribution
The distribution of scopolamine is not well characterized. It crosses the placenta and the blood brain barrier and may be reversibly bound to plasma proteins.

Elimination

Metabolism and Excretion
Scopolamine is metabolized and conjugated with less than 5% of the total dose appearing unchanged in the urine. The enzymes responsible for metabolizing scopolamine are unknown. The exact elimination pattern of scopolamine has not been determined. Following transdermal system removal, plasma concentrations of scopolamine decline in a log linear fashion with an observed half-life of 9.5 hours. Less than 10% of the total dose is excreted in the urine as the parent drug and metabolites over 108 hours.

Drug Interaction Studies

An in vitro study using human hepatocytes examined the induction of CYP1A2 and CYP3A4 by scopolamine. Scopolamine did not induce CYP1A2 and CYP3A4 isoenzymes at the concentrations up to 10 nM. In an in vitro study using human liver microsomes which evaluated the inhibition of CYP1A2, 2C8, 2C9, 2C19, 2D6 and 3A4, scopolamine did not inhibit these cytochrome P450 isoenzymes at the concentrations up to 1 micromolar. No in vivo drug-drug interaction studies have been conducted.

13 NONCLINICAL TOXICOLOGY

13.1 Carcinogenesis, Mutagenesis, Impairment of Fertility

No long-term studies in animals have been conducted to evaluate the carcinogenic potential of scopolamine. The mutagenic potential of scopolamine has not been evaluated.

Fertility studies were performed in female rats and revealed no evidence of impaired fertility or harm to the fetus due to scopolamine hydrobromide administered by daily subcutaneous injection. Maternal body weights were reduced in the highest-dose group (plasma level approximately 500 times the level achieved in humans using a transdermal system). However, fertility studies in male animals were not performed.

14 CLINICAL STUDIES

14.1 Prevention of Motion Sickness

In 195 adult subjects of different racial origins who participated in clinical efficacy studies at sea or in a controlled motion environment, there was a 75% reduction in the incidence of motion-induced nausea and vomiting. TRANSDERM SCŌP was applied from 4 to 16 hours prior to the onset of motion in these studies.

14.2 Prevention of Post-Operative Nausea and Vomiting

A clinical efficacy study evaluated 168 adult female patients undergoing gynecological surgery with anesthesia and opiate analgesia. Patients received TRANSDERM SCŌP or placebo applied approximately 11 hours before anesthesia/opiate analgesia. No retching/vomiting during the 24-hour post-operative period was reported in 79% of those treated with TRANSDERM SCŌP compared to 72% of those receiving placebo. When the need for additional antiemetic medication was assessed during the same period, there was no need for medication in 89% of patients treated with TRANSDERM SCŌP as compared to 72% of placebo-treated patients.

16 HOW SUPPLIED/STORAGE AND HANDLING

TRANSDERM SCŌP (scopolamine transdermal system) 1 mg/3 days is available as the following:

Cartons of 4, 10, and 24 transdermal systems, packaged into individual foil pouches.

- Carton of 4 transdermal systems. NDC 10019-008-04
- Carton of 10 transdermal systems. NDC 10019-008-10
- Carton of 24 transdermal systems. NDC 10019-008-24

Store at controlled room temperature between 20°C to 25°C (68°F to 77°F).

Store pouch(es) in an upright position.

Do not bend or roll pouch(es).

Wash hands thoroughly with soap and water immediately after handling the transdermal system. Avoid touching the system during the treatment. Upon removal, fold the used transdermal system in half with the sticky side together, and discard in household trash in a manner that prevents accidental contact or ingestion by children, pets or others. Wash the hands and application site with soap and water after transdermal system removal [see Dosage and Administration (2.1), Warnings and Precautions (5.7)].

17 PATIENT COUNSELING INFORMATION

Advise the patient to read the FDA-approved patient labeling (Patient Information and Instructions for Use).

Administration Instructions

Counsel patients on how to apply and remove the transdermal system [see Dosage and Administration (2.1)]:

- Only wear one transdermal system at any time.
- Do not cut the transdermal system.
- Apply the transdermal system to the skin in the postauricular (hairless area behind one ear) area.
- After the transdermal system is applied on the dry skin behind the ear, wash hands thoroughly with soap and water and dry hands.
- If the transdermal system becomes displaced, discard the transdermal system, and apply a new transdermal system on the hairless area behind the other ear.
- Once the transdermal system has been affixed, avoid touching or applying pressure to the transdermal system, since pressure exerted on it may cause scopolamine to ooze out at the edge.
- Upon removal, fold the used transdermal system in half with the sticky side together, and discard in household trash in a manner that prevents accidental contact or ingestion by children, pets or others.
- Wash the hands and application site with soap and water after transdermal system removal.

Patients with Open-Angle Glaucoma

Advise patients with open-angle glaucoma to remove the TRANSDERM SCŌP transdermal system immediately and contact their healthcare provider if they experience symptoms of acute angle closure glaucoma, including pain and reddening of the eyes, accompanied by dilated pupils, blurred vision and/or seeing halos around lights [see Warnings and Precautions (5.1)].

Neuropsychiatric Adverse Reactions

- Advise patients that psychiatric adverse reactions may occur, especially in patients with a past psychiatric history or in those receiving other drugs also associated with psychiatric effects, and to report to their healthcare provider any new or worsening psychiatric symptoms.
- Advise patients to discontinue TRANSDERM SCŌP and contact a healthcare provider immediately if they experience a seizure.
- Advise patients, especially elderly patients, that cognitive impairment may occur during treatment with TRANSDERM SCŌP, especially in those receiving other drugs also associated with CNS effects, and to report to their healthcare provider if they develop signs or symptoms of cognitive impairment such as hallucinations, confusion or dizziness.
- Inform patients not to operate motor vehicles or other dangerous machinery or participate in underwater sports until they are reasonably certain that TRANSDERM SCŌP does not affect them adversely [see Warnings and Precautions (5.2)].

Decreased Gastrointestinal Motility and Urinary Retention

Instruct patients to remove the transdermal system if they develop symptoms of intestinal obstruction (abdominal pain, nausea or vomiting) or any difficulties in urinating [see Warnings and Precautions (5.4)].

Hyperthermia

Inform patients that TRANSDERM SCŌP can increase body temperature and reduce sweating, which may result in hyperthermia and be exacerbated by exposure to external heat sources or high environmental temperature. Geriatric patients may be more susceptible to these effects. Advise patients if body temperature increases, or they are not sweating in warm environmental conditions, remove the transdermal system, and contact their healthcare provider. Symptoms may persist after removal of the transdermal system [see Warnings and Precautions (5.5)].

Drug Withdrawal/Post-Removal Symptoms

Inform patients that if they remove the TRANSDERM SCŌP transdermal system after several days of use, withdrawal symptoms may occur and to seek immediate medical care if they develop severe symptoms after removing TRANSDERM SCŌP [see Warnings and Precautions (5.6)].

Blurred Vision

Inform patients that temporary dilation of the pupils and blurred vision may occur if TRANSDERM SCŌP comes in contact with the eyes. Instruct patients to wash their hands thoroughly with soap and water immediately after handling the transdermal system, do not touch the system while wearing it, and wash hands and the application site with soap and water after transdermal system removal [see Dosage and Administration (2.1), see Warnings and Precautions (5.7)].

MRI Skin Burns

Instruct patients to remove the TRANSDERM SCŌP transdermal system before undergoing an MRI [see Warnings and Precautions (5.8)].

Marketed by: Baxter Healthcare Corporation
Deerfield, IL 60015 USA
For Product Inquiry 1 800 ANA DRUG (1-800-262-3784)

Trademarks are owned by or licensed to Baxter International Inc. or its subsidiaries.
07-19-00-9783

PATIENT INFORMATION

TRANSDERM SCŌP (trans-derm skōp)

(scopolamine transdermal system)

Read this Patient Information before you start using TRANSDERM SCŌP and each time you get a refill. There may be new information. This information does not take the place of talking to your doctor about your medical condition or your treatment.

What is TRANSDERM SCŌP?

TRANSDERM SCŌP is a prescription medicine used for adults to help prevent:

- nausea and vomiting from motion sickness
- nausea and vomiting from anesthesia or taking opioid pain medicines after surgery

It is not known if TRANSDERM SCŌP is safe and effective in children.

Who should not use TRANSDERM SCŌP?

Do not use TRANSDERM SCŌP if you:

- have an eye problem called angle closure glaucoma.
- are allergic to scopolamine, belladonna alkaloids or any of the ingredients in TRANSDERM SCŌP. See the end of this Patient Information leaflet for a list of the ingredients in TRANSDERM SCŌP. Ask your doctor if you are not sure.

What should I tell my doctor before using TRANSDERM SCŌP?

Before you use TRANSDERM SCŌP, tell your doctor about all of your medical conditions, including if you:

- have glaucoma (increased pressure in the eye).
- have a history of seizures or psychosis.
- have problems with your stomach or intestines.
- have trouble urinating.
- are scheduled to have a gastric secretion test.
- have liver or kidney problems.
- are pregnant or plan to become pregnant. It is not known if TRANSDERM SCŌP can harm your unborn baby.
- are breastfeeding or plan to breastfeed. TRANSDERM SCŌP can pass into your breast milk. Talk to your doctor about the best way to feed your baby if you use TRANSDERM SCŌP.

Tell your doctor about all the medicines you take, including prescription and over-the-counter medicines, vitamins and herbal supplements. TRANSDERM SCŌP may affect the way other medicines work, and other medicines may affect how TRANSDERM SCŌP works. Medicines that you take by mouth may not be absorbed well while you use TRANSDERM SCŌP.

Especially tell your doctor if you take:

- a sedative, hypnotic, opioid or anxiolytic (medicines that make you sleepy)
- an antidepressant medicine
- an anticholinergic medicine, such as an allergy or cold medicine, a medicine to treat bladder or bowel spasms, certain asthma medicines, or other medicines for motion sickness

Ask your doctor if you are not sure if your medicine is one that is listed above.

Know the medicines you take. Keep a list of them and show it to your doctor or pharmacist when you get a new medicine.

How should I use TRANSDERM SCŌP?

- See the detailed Instructions for Use for information about how to use TRANSDERM SCŌP at the end of this Patient Information leaflet.
- It is important that you apply TRANSDERM SCŌP exactly as your doctor tells you to.
- Your doctor may change your TRANSDERM SCŌP dose. Do not change your TRANSDERM SCŌP dose without talking to your doctor.
- Wear only one TRANSDERM SCŌP at any time.
- If you use too much TRANSDERM SCŌP, call your doctor or Poison Help line at 1-800-222-1222, or go to the nearest hospital emergency room right away.

What should I avoid while using TRANSDERM SCŌP?

- You should not drink alcohol while using TRANSDERM SCŌP. It can increase your chances of having serious side effects.
- You should not drive, operate heavy machinery, or do other dangerous activities until you know how TRANSDERM SCŌP affects you.
- You should not use TRANSDERM SCŌP during a Magnetic Resonance Imaging scan (MRI). Remove TRANSDERM SCŌP before undergoing an MRI. It can cause your skin to burn.
- You should be careful if you use TRANSDERM SCŌP while you participate in watersports because you may feel lost or confused (disoriented).
- Limit contact with water while swimming and bathing because TRANSDERM SCŌP may fall off. If TRANSDERM SCŌP falls off, throw it away and apply a new one on the hairless area behind your other ear.

What are the possible side effects of TRANSDERM SCŌP?

TRANSDERM SCŌP may cause serious side effects, including:

- angle closure glaucoma. If you have open angle glaucoma and use TRANSDERM SCŌP, remove TRANSDERM SCŌP and call a doctor right away if you feel pain or discomfort, have blurred vision, or see halos or colored images around lights and reddening of your eyes.
- worsening of seizures. Tell your doctor about any worsening of seizures while using TRANSDERM SCŌP.
- an unusual reaction called acute psychosis. Tell your doctor if you have any of these symptoms:
  - confusion
  - agitation
  - rambling speech
  - hallucinations (seeing or hearing things that are not there)
  - paranoid behaviors and delusions (false belief in something)
If you experience any of the above symptoms, your doctor may stop your treatment with TRANSDERM SCŌP. If your symptoms continue and they are severe, get medical help.
- worsening of your preeclampsia during pregnancy. Some pregnant women with severe preeclampsia have had seizures after getting scopolamine by injection in the muscle (intramuscular) or injection in the vein (intravenous).
- difficulty urinating.
- difficulties in food passing from the stomach to the small intestines, which may cause abdominal pain, nausea or vomiting.
- increased body temperature (hyperthermia) and a decrease in sweating. If you have a high body temperature or if you are not sweating in warm conditions, remove the transdermal system and contact your doctor. Elderly people may be at greater risk for these side effects.
- withdrawal symptoms after removing TRANSDERM SCŌP after using it for several days. Some people may have certain symptoms such as difficulty with balance, dizziness, nausea, vomiting, stomach cramps, sweating, confusion, muscle weakness, low heart rate or low blood pressure that could start 24 hours or more after removing TRANSDERM SCŌP. Call your doctor right away if your symptoms become severe.
- temporary increase in the size of your pupil and blurry vision, especially if TRANSDERM SCŌP comes in contact with your eyes.
- skin burns at the site of TRANSDERM SCŌP. This can happen during a medical test called a Magnetic Resonance Imaging scan (MRI). TRANSDERM SCŌP contains aluminum and should be removed from your skin before you have an MRI.

The most common side effects of using TRANSDERM SCŌP include:

- dry mouth

- blurred vision or eye problems

- feeling sleepy or drowsy

- disorientation (confusion)

- dizziness

- feeling agitated or irritable

- pharyngitis (sore throat)

Tell your doctor if you have any side effect that bothers you or that does not go away. These are not all the possible side effects of TRANSDERM SCŌP.

Call your doctor for medical advice about side effects. You may report side effects to FDA at 1-800-FDA-1088.

General information about the safe and effective use of TRANSDERM SCŌP.

Medicines are sometimes prescribed for purposes other than those listed in a patient information leaflet. Do not use TRANSDERM SCŌP for a condition for which it was not prescribed. Do not give TRANSDERM SCŌP to other people, even if they have the same symptoms you have. It may harm them.

You can ask your pharmacist or doctor for information about TRANSDERM SCŌP that is written for health professionals.

What are the ingredients in TRANSDERM SCŌP?

Active ingredient: scopolamine

Inactive ingredients: crospovidone, isopropyl palmitate, light mineral oil, polyisobutylene, ethylene vinyl acetate copolymer and aluminized polyester film
Marketed by: Baxter Healthcare Corporation,

Deerfield, IL 60015 USA

Trademarks are owned by or licensed to Baxter International Inc. or its subsidiaries.
For more information, go to www.transdermscop.com or call Baxter Healthcare Corporation at 1 800 ANA DRUG (1-800-262-3784).

INSTRUCTIONS FOR USE

TRANSDERM SCŌP (trans-derm skōp)
(scopolamine transdermal system)

Read this Instructions for Use before you start using TRANSDERM SCŌP and each time you get a refill. There may be new information. This information does not take the place of talking to your doctor about your medical condition or your treatment.

Information about TRANSDERM SCŌP:

- TRANSDERM SCŌP is a tan-colored, circle shaped transdermal system (patch) with “SCOP1 mg/3 days” printed on it.
- Wear only one TRANSDERM SCŌP at any time.
- Do not cut TRANSDERM SCŌP.

To help prevent nausea and vomiting from motion sickness:

- Apply one TRANSDERM SCŌP to your skin on a hairless area behind one ear at least 4 hours before the activity to prevent nausea and vomiting.
- If the treatment is needed for longer than 3 days, remove TRANSDERM SCŌP from the hairless area behind your ear. Get a new TRANSDERM SCŌP and place it on the hairless area behind your other ear.

To help prevent nausea and vomiting after surgery:

- Follow your doctor’s instructions about when to apply TRANSDERM SCŌP before your scheduled surgery.
- TRANSDERM SCŌP should be left in place for 24 hours after surgery. After 24 hours, TRANSDERM SCŌP should be removed and thrown away.

How to use TRANSDERM SCŌP:

Inside the TRANSDERM SCŌP package, you will find one TRANSDERM SCŌP. An imprinted, tan backing membrane with a metallic (silver) sticky surface is adhered to a clear, disposable release liner (See Figure 1).

1. Select a hairless area of skin behind one of your ears. Avoid areas on your skin that may have cuts, pain or tenderness. Wipe the area of your skin with a clean, dry tissue.
2. Cut along the dashed line on the TRANSDERM SCŌP package to open (See Figure 2).

3. Remove the clear plastic backing from the tan-colored round TRANSDERM SCŌP (See Figure 3).

4. Do not touch the metallic adhesive (sticky) surface on TRANSDERM SCŌP with your hands (See Figure 4).

5. Apply the metallic adhesive surface of TRANSDERM SCŌP firmly to the dry area of skin behind your ear. The imprinted, tan colored side of the transdermal system should be facing up and showing (See Figure 5). After placement of TRANSDERM SCŌP, avoid touching or applying pressure to the transdermal system while it is being worn because applying pressure may cause scopolamine to ooze out at the edge. Wash your hands with soap and water right away after applying TRANSDERM SCŌP, so that any medicine from TRANSDERM SCŌP that gets on your hands will not get into your eyes.

How to remove TRANSDERM SCŌP:

After removing TRANSDERM SCŌP, be sure to wash your hands and the area behind your ear thoroughly with soap and water. Please note that the used TRANSDERM SCŌP will still contain some of the active ingredient after use. To avoid accidental contact or ingestion by children, pets or others, fold the used TRANSDERM SCŌP in half with the sticky side together. Throw away (dispose of) TRANSDERM SCŌP in the household trash out of the reach of children, pets or others.

How should I store TRANSDERM SCŌP?

- Store TRANSDERM SCŌP at room temperature between 68°F and 77°F (20°C and 25°C) until you are ready to use it.
- Store TRANSDERM SCŌP in an upright position.
- Do not bend or roll TRANSDERM SCŌP.

Keep TRANSDERM SCŌP and all medicines out of reach of children.

The Patient Information and Instructions for Use have been approved by the U.S. Food and Drug Administration
Revised: 06/2025

07-19-00-8984

PRINCIPAL DISPLAY PANEL

Container Label

Each transdermal system contains 1.3 mg scopolamine formulated to deliver in vivo
approximately 1 mg over 3 days. The inactive components are
crospovidone, isopropyl palmitate, light mineral oil, polyisobutylene, ethylene
vinyl acetate copolymer and aluminized polyester film.
Dosage and Administration:
1. Before applying transdermal system, wash and dry hands thoroughly.
2. Use only one transdermal system at a time. Do not cut the transdermal
system.
3. Remove and discard clear plastic backing from transdermal system.
4. Apply to the hairless area behind one ear as indicated in accompanying
prescribing information.
5. Wash and dry hands thoroughly after application.
See accompanying prescribing information for details.

Keep this and all medication out of reach of children.

FOIL-SEALED FOR YOUR PROTECTION.
DO NOT USE IF SEAL IS BROKEN.
Marketed by
Baxter Healthcare Corporation,
Deerfield,
IL 60015 USA

Baxter Logo
Rev 11-24

BARCODE
(01)00310019008011

1002653
07-07-00-2612

CUT ALONG LINE TO OPEN

Rx only

NDC 10019-008-01

TRANSDERM SCŌP
(scopolamine)
TRANSDERMAL SYSTEM, 1 mg/3 days

Contents: 1 Transdermal System

Caution:
WASH HANDS IMMEDIATELY AFTER APPLICATION.
CONTACT WITH EYES MAY CAUSE IRRITATION.
May cause drowsiness, blurred vision. To avoid possible burns, remove Transderm
Scōp before undergoing an MRI (Magnetic Resonance Imaging) procedure.

Store upright at controlled room temperature between 20°C and 25°C (68°F and 77°F)

TRANSDERM SCŌP

Image
07-07-00-3156

Carton Label

TRANSDERM SCŌP
(scopolamine)
TRANSDERMAL SYSTEM,1 mg/3 days

4 Transdermal
Systems
Multipack

Each transdermal system contains 1.3 mg scopolamine formulated to deliver
in vivo approximately 1 mg over 3 days. The inactive components are crospovidone,
isopropyl palmitate, light mineral oil, polyisobutylene, ethylene vinyl acetate
copolymer and aluminized polyester film.
Dosage and Administration:
1. Before applying transdermal system, wash and dry hands thoroughly.
2. Use only one transdermal system at a time.Do not cut the transdermal
system.
3. Remove and discard clear plastic backing from transdermal system.
4. Apply to the hairless area behind one ear as indicated in accompanying
prescribing information.
5. Wash your hands with soap and water after application.
See accompanying prescribing information for details.

Caution: May cause drowsiness, blurred vision. To avoid possible burns, remove
Transderm Scōp before undergoing MRI (Magnetic Resonance Imaging)
procedure.
Keep this and all medication out of reach of children.
Store upright at controlled room temperature between 20°C-25°C (68°F-77°F).

Baxter Logo

Marketed by Baxter Healthcare Corporation
Deerfield, IL 60015 USA

Trademarks are owned by or licensed to Baxter
International Inc. or its subsidiaries.

AVUS0104

FOIL-SEALED
FOR YOUR PROTECTION.
DO NOT USE
IF SEAL IS BROKEN.

Rev 11-24
1002654

GTIN 20310019008046
SN XXXXXXXXXXXX
LOT XXXXX
EXP YYYY-MM-DD

NDC 10019-008-04

TRANSDERM SCŌP
(scopolamine)
TRANSDERMAL SYSTEM,
1 mg/3 days

Formulated delivery
of approximately
1 mg over three days

4 Transdermal
Systems
Multipack

RX ONLY

TRANSDERM SCŌP
Image

Barcode
(01) 20310019008046

Transderm Scōp
(scopolamine)
TRANSDERMAL SYSTEM, 1 mg/3 days
4 Transdermal Systems Multipack
For Product Inquiry
1 800 ANA DRUG
(1-800-262-3784)

TRANSDERM SCŌP
(scopolamine)
TRANSDERMAL SYSTEM, 1 mg/3 days

4 Transdermal
Systems Multipack
For Product Inquiry
1 800 ANA DRUG
(1-800-262-3784)
07-03-00-1416

Carton Label

TRANSDERM SCŌP
(scopolamine)
TRANSDERMAL SYSTEM,1 mg/3 days

24 Transdermal Systems
Multipack

TRANSDERM SCŌP
(scopolamine)
TRANSDERMAL SYSTEM, 1 mg/3 days

24 Transdermal
Systems
Multipack

Each transdermal system contains 1.3 mg scopolamine formulated to deliver
in vivo approximately 1 mg over 3 days. The inactive components are crospovidone,
isopropyl palmitate, light mineral oil, polyisobutylene, ethylene vinyl acetate
copolymer and aluminized polyester film.
Dosage and Administration:
1. Before applying transdermal system, wash and dry hands thoroughly.
2. Use only one transdermal system at a time.Do not cut the transdermal
system.
3. Remove and discard clear plastic backing from transdermal system.
4. Apply to the hairless area behind one ear as indicated in accompanying
prescribing information.
5. Wash your hands with soap and water after application.
See accompanying prescribing information for details.
Caution: May cause drowsiness, blurred vision. To avoid possible burns, remove
Transderm Scōp before undergoing MRI (Magnetic Resonance Imaging)
procedure.
Keep this and all medication out of reach of children.
Store upright at controlled room temperature between 20°C-25°C (68°F-77°F).

Baxter Logo

Marketed by Baxter Healthcare Corporation
Deerfield, IL 60015 USA

Trademarks are owned by or licensed to Baxter
International Inc. or its subsidiaries.

AVUS0124

FOIL-SEALED
FOR YOUR PROTECTION.
DO NOT USE
IF SEAL IS BROKEN.

Rev 11-24
1002656

Transderm Scōp (scopolamine)
TRANSDERMAL SYSTEM,
1 mg/3 days
24 Transdermal Systems Multipack
For Product Inquiry
1 800 ANA DRUG
(1-800-262-3784)

GTIN 20310019008244
SN XXXXXXXXXXXX
LOT XXXXX
EXP YYYY-MM-DD

NDC 10019-008-24

TRANSDERM SCŌP
(scopolamine)
TRANSDERMAL SYSTEM,
1 mg/3 days

Formulated delivery
of approximately
1 mg over three days

24 Transdermal
Systems
Multipack

RX ONLY

TRANSDERM SCŌP
Image

Barcode
(01) 20310019008244

07-03-00-1534

TRANSDERM SCŌP
(scopolamine)
TRANSDERMAL SYSTEM, 1 mg/3 days

24 Transdermal Systems Multipack
For Product Inquiry
1 800 ANA DRUG
(1-800-262-3784)
07-03-00-1416

Carton Label

TRANSDERM SCŌP
(scopolamine)
TRANSDERMAL SYSTEM,1 mg/3 days

10 Transdermal
Systems
Multipack

TRANSDERM SCŌP
(scopolamine)
TRANSDERMAL SYSTEM, 1 mg/3 days

10 Transdermal
Systems
Multipack

Each transdermal system contains 1.3 mg scopolamine formulated to deliver
in vivo approximately 1 mg over 3 days. The inactive components are crospovidone,
isopropyl palmitate, light mineral oil, polyisobutylene, ethylene vinyl acetate
copolymer and aluminized polyester film.
Dosage and Administration:
1. Before applying transdermal system, wash and dry hands thoroughly.
2. Use only one transdermal system at a time.Do not cut the transdermal
system.
3. Remove and discard clear plastic backing from transdermal system.
4. Apply to the hairless area behind one ear as indicated in accompanying
prescribing information.
5. Wash your hands with soap and water after application.
See accompanying prescribing information for details.
Caution: May cause drowsiness, blurred vision. To avoid possible burns, remove
Transderm Scōp before undergoing MRI (Magnetic Resonance Imaging)
procedure.
Keep this and all medication out of reach of children.
Store upright at controlled room temperature between 20°C-25°C (68°F-77°F).

Baxter Logo

Marketed by Baxter Healthcare Corporation
Deerfield, IL 60015 USA

Trademarks are owned by or licensed to Baxter
International Inc. or its subsidiaries.

AVUS0110

FOIL-SEALED
FOR YOUR PROTECTION.
DO NOT USE
IF SEAL IS BROKEN.

Rev 11-24
1002655

Transderm Scōp (scopolamine)
TRANSDERMAL SYSTEM, 1 mg/3 days
10 Transdermal Systems Multipack
For Product Inquiry
1 800 ANA DRUG
(1-800-262-3784)

GTIN 20310019008107
SN XXXXXXXXXXXX
LOT XXXXX
EXP YYYY-MM-DD

NDC 10019-008-10

TRANSDERM SCŌP
(scopolamine)
TRANSDERMAL SYSTEM,
1 mg/3 days

Formulated delivery
of approximately
1 mg over three days

10 Transdermal
Systems
Multipack

RX ONLY

TRANSDERM SCŌP
Image

Barcode
(01) 20310019008107

TRANSDERM SCŌP
(scopolamine)
TRANSDERMAL SYSTEM, 1 mg/3 days

10 Transdermal Systems Multipack
For Product Inquiry
1 800 ANA DRUG
(1-800-262-3784)
07-03-00-1416